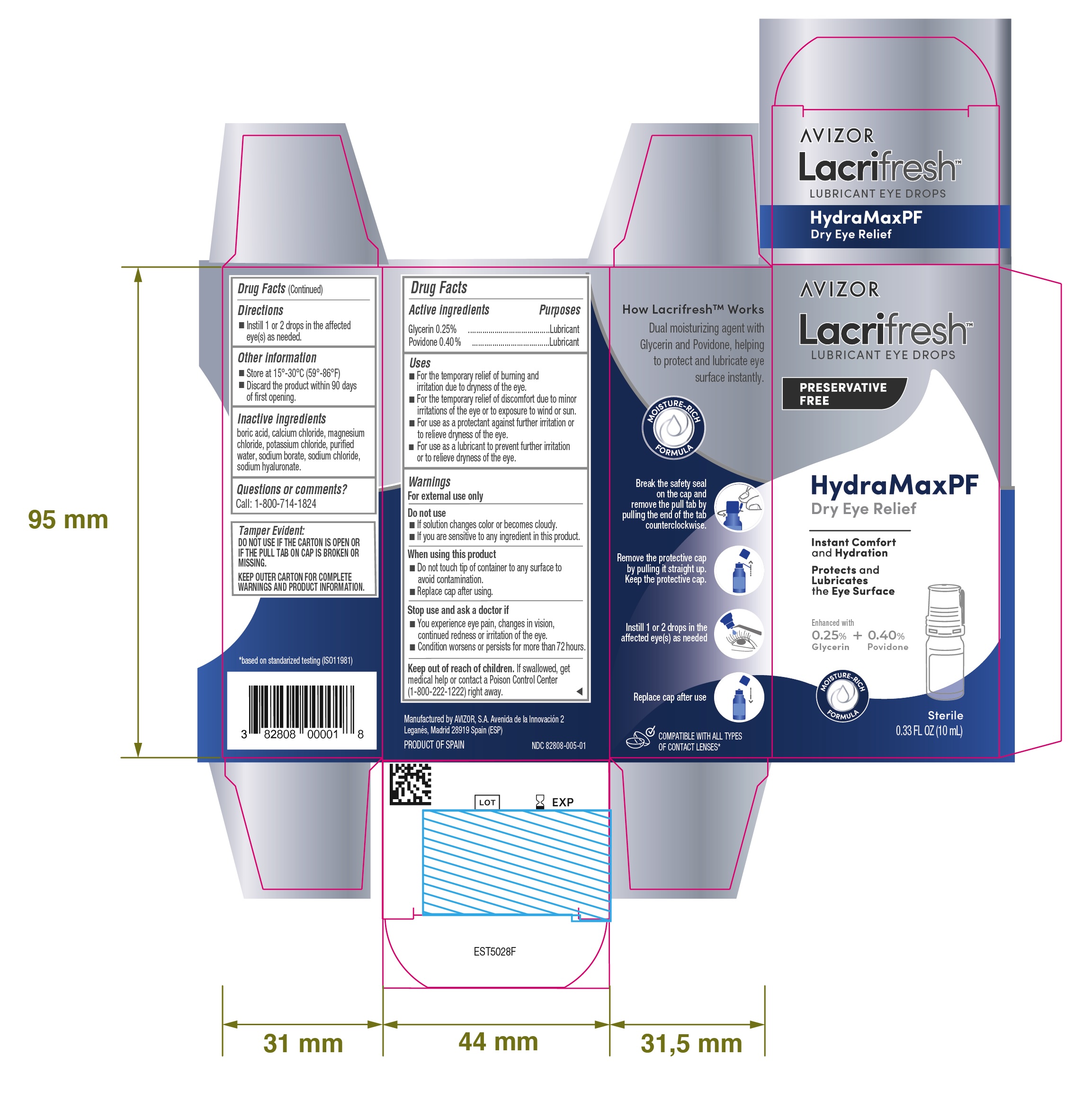 DRUG LABEL: LACRIFRESH HYDRAMAXPF
NDC: 82808-005 | Form: SOLUTION/ DROPS
Manufacturer: AVIZOR, S.A.
Category: otc | Type: HUMAN OTC DRUG LABEL
Date: 20251027

ACTIVE INGREDIENTS: GLYCERIN 0.25 g/100 mL; POVIDONE 0.4 g/100 mL
INACTIVE INGREDIENTS: CALCIUM CHLORIDE; MAGNESIUM CHLORIDE; SODIUM BORATE; SODIUM CHLORIDE; POTASSIUM CHLORIDE; BORIC ACID; SODIUM HYALURONATE

LACRIFRESH HYDRAMAXPF

Active ingredients | Purposes
Glycerin 0.25% | Lubricant
Povidone 0.40% | Lubricant

INDICATIONS AND USAGE

PURPOSE

- For the temporary relief of burning and irritation due to dryness of the eye
- For the temporary relief of discomfort due to minor irritations of the eye or to exposure to wind or sun
- For use as a protectant against further irritation or to relief dryness of the eye
- For use as a lubricant to prevent further irritation or to relief dryness of the eye

WARNINGS

For external use only

Do not use

- If solution changes color or becomes cloudy
- If you are sensitive to any ingredient in this product

When using this product

- Do not touch tip of container to any surface to avoid contamination
- Replace cap after using

Stop use and ask a doctor if

- You experience eye pain, changes in vision, continued redness or irritation of the eye
- Condition worsens or persists for more than 72 hours

Keep out of reach of children

If swallowed, get medical help or contact a Poison Control Center (1-800-222-1222) right away.

Directions

- Instill 1 or 2 drops in the affected eye(s) as needed

Other information

- Store at 15º-30ºC (59º-86ºF)
- Discard the product within 90 days of first opening

Inactive ingredients

boric acid, calcium chloride, magnesium chloride, potassium chloride, purified water, sodium borate, sodium chloride, sodium hyaluronate

Questions or comments?

Call: 1-800-714-1824

PACKAGE LABEL

AVIZOR

Lacrifresh

LUBRICANT EYE DROPS

PRESERVATIVE FREE

HydraMaxPF

Dry Eye Relief

Instant Comfort and Hydration

Protects and Lubricates the Eye Surface

Enhanced with

0.25% Glycerin + 0.40% Povidone

MOISTURE-RICH FORMULA

Sterile

0.33 FL OZ (10 mL)